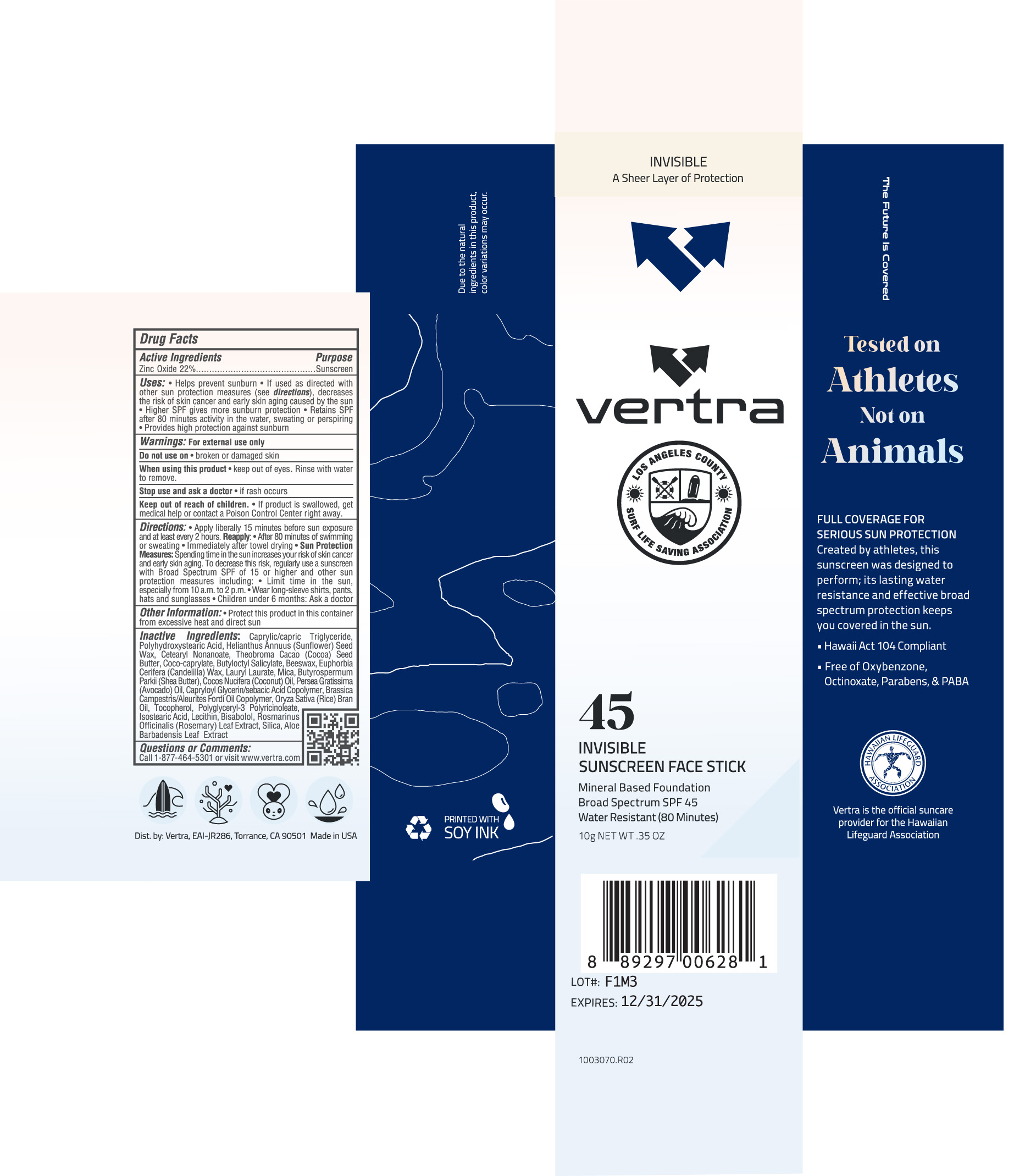 DRUG LABEL: Vertra Invisible Sunscreen Face Stick Broad Spectrum SPF 45
NDC: 71014-041 | Form: STICK
Manufacturer: Eai-jr 286, Inc
Category: otc | Type: HUMAN OTC DRUG LABEL
Date: 20250318

ACTIVE INGREDIENTS: ZINC OXIDE 22 g/100 g
INACTIVE INGREDIENTS: MICA; BUTYLOCTYL SALICYLATE; EUPHORBIA CERIFERA (CANDELILLA) WAX; CAPRYLIC/CAPRIC TRIGLYCERIDE; COCO-CAPRYLATE; BUTYROSPERMUM PARKII (SHEA) BUTTER; CAPRYLOYL GLYCERIN/SEBACIC ACID COPOLYMER (2000 MPA.S); TOCOPHEROL; ROSEMARY; BEESWAX; LAURYL LAURATE; SILICA; RICE BRAN OIL; BISABOLOL; POLYHYDROXYSTEARIC ACID (2300 MW); ALOE VERA LEAF; HELIANTHUS ANNUUS (SUNFLOWER) SEED WAX; ISOSTEARIC ACID; AVOCADO OIL; LECITHIN, SOYBEAN; POLYGLYCERYL-3 PENTARICINOLEATE; CETEARYL NONANOATE; COCONUT OIL; THEOBROMA CACAO (COCOA) SEED BUTTER

Vertra Invisible Sunscreen Face Stick Broad Spectrum SPF 45 LA Lifeguard

Active Ingredients Purpose

Zinc Oxide 22% ....Sunscreen

Uses

- Helps prevent sunburn
- If used as directed with other sun protection measures (see Directions), decreases the risk of skincancer and early skin aging caused by the sun

Keep out of reach of children

- If product is swallowed, get medical help or contact a Poison Control Center right away.

Stop use and ask a doctor

- if rash occurs

Warnings: For external use only

Do not use on

- broken or damaged skin

When using this product

- keep out of eyes. Rinse with water to remove

Directions

- Apply liberally 15 minutes before sun exposure

Reapply

- After 80 minutes of swimming or sweating
- Immediately after towel drying

Sun Protection Measures: Spending time in the sun increases your risk of skin cancer and early skin aging. To decrease this risk, regularly use a sunscreen with a Broad Spectrum SPF value of 15 or higher and other sun protection measures including:

- Limit time in the sun, especially from 10 a.m.- 2 p.m.
- Wear long-sleeved shirts, pants, hats and sunglasses
- Children under 6 months: Ask a doctor

INACTIVE INGREDIENT

Inactive Ingredients: Caprylic/capric Triglyceride, Polyhydroxystearic Acid, Helianthuus Annuus (Sunflower) Seed Wax, Cetearyl Nonanoate, Theobroma Cacao (Cocoa) Seed Butter, Coco-caprylate, Butyloctyl Salicylate, Beeswax, Euphorbia Cerifera (Candelilla) Wax, Lauryl Laurate, Mica, Butyrospermum Parkii (Shea Butter), Cocos Nucifera (coconut) Oil, Persea Gratissima (Avocado) Oil, Capryloyl Glycerin/sebacic Acid Copolymer, Brassica Campestris/Aleurites Fordi Oil Coplymer, Oryza Sativa (Rice) Bran Oil,

Tocopherol, Polyglyceryl-3 Polyricinoleate, Isostearic Acid, Lecithin, Bisabolol, Rosmarinus Officinalis (Rosemary) Leaf Extract, Silica, Aloe Barbadensis Leaf Extract

PACKAGE LABEL

vertra

45

Invisible

Sunscreen Face Stick

Mineral Based Foundation

Broad Spectrum SPF 45

Water Resistant (80 minutes)

10g NET WT .35 OZ